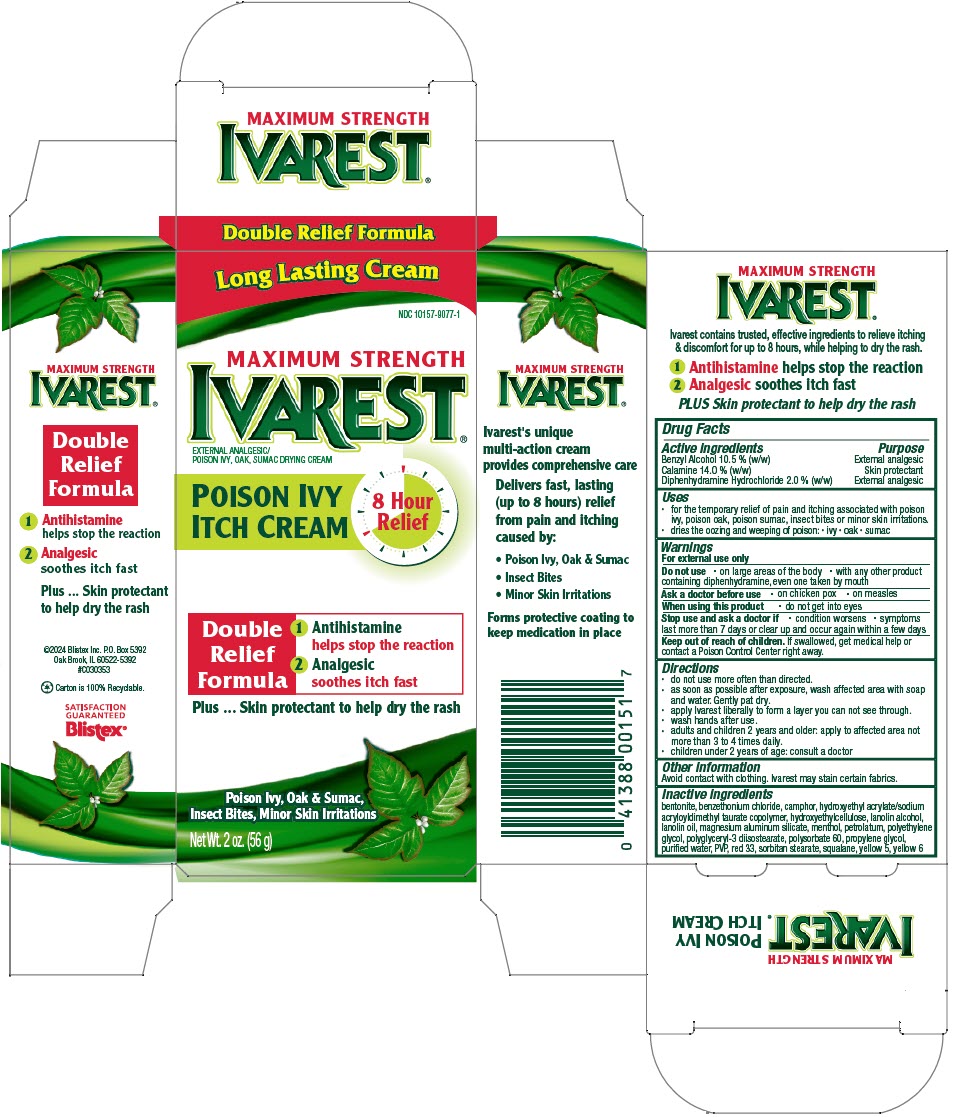 DRUG LABEL: Ivarest
NDC: 10157-9077 | Form: CREAM
Manufacturer: Blistex Inc
Category: otc | Type: HUMAN OTC DRUG LABEL
Date: 20240709

ACTIVE INGREDIENTS: Zinc Oxide 14 g/100 g; Benzyl Alcohol 10.5 g/100 g; Diphenhydramine Hydrochloride 2 g/100 g
INACTIVE INGREDIENTS: bentonite; benzethonium chloride; lanolin alcohols; lanolin oil; magnesium aluminum silicate; MENTHOL, UNSPECIFIED FORM; POLYETHYLENE GLYCOL, UNSPECIFIED; petrolatum; polyethylene glycol 200; polyglyceryl-3 diisostearate; polysorbate 60; propylene glycol; water; D&C red no. 33; sorbitan monostearate; squalane; FD&C yellow no. 5; FD&C yellow no. 6; camphor (synthetic); povidone-iodine; HYDROXYETHYL ACRYLATE/SODIUM ACRYLOYLDIMETHYL TAURATE COPOLYMER (100000 MPA.S AT 1.5%)

Ivarest®

Drug Facts

ACTIVE INGREDIENT

Active ingredients | Purpose
Calamine 14.0 % (w/w) | Skin protectant
Benzyl Alcohol 10.5 % (w/w) | External analgesic
Diphenhydramine Hydrochloride 2.0 % (w/w) | External analgesic

Uses

- for the temporary relief of pain and itching associated with poison ivy, poison oak, poison sumac, insect bites or minor skin irritations.
- dries the oozing and weeping of poison:
  - ivy
  - oak
  - sumac

Warnings

For external use only

Do not use

- on large areas of the body
- with any other product containing diphenhydramine, even one taken by mouth

Ask a doctor before use

- on chicken pox
- on measles

When using this product

- do not get into eyes.

Stop use and ask a doctor if

- condition worsens
- symptoms last more than 7 days or clear up and occur again within a few days

Keep out of reach of children. If swallowed, get medical help or contact a Poison Control Center right away.

Directions

- do not use more often than directed
- as soon as possible after exposure, wash affected area with soap and water (or Ivarest Poison Ivy Cleansing Foam). Gently pat dry.
- apply Ivarest liberally to form a layer you can not see through.
- adults and children 2 years and older: apply to affected area not more than 3 to 4 times daily. Children under 2 years of age: consult a doctor.

Other information

Avoid contact with clothing. Ivarest may stain certain fabrics.

Inactive ingredients

bentonite, benzethonium chloride, camphor, hydroxyethyl acrylate/sodium acryloyldimethyl taurate copolymer, hydroxyethylcellulose, lanolin alcohol, lanolin oil, magnesium aluminum silicate, menthol, petrolatum, polyethylene glycol, polyglyceryl-3 diisostearate, polysorbate 60, propylene glycol, purified water, PVP, red 33, sorbitan stearate, squalane, yellow 5, yellow 6

PRINCIPAL DISPLAY PANEL - 56 g Tube Carton

Long Lasting Cream

NDC 10157-9077-1

MAXIMUM STRENGTH
IVAREST®
EXTERNAL ANALGESIC/
POISON IVY, OAK, SUMAC DRYING CREAM

POISON IVY
ITCH CREAM

8 Hour
Relief

Double
Relief
Formula

1 Antihistamine
  helps stop the reaction
2 Analgesic
  soothes itch fast

Plus ... Skin protectant to help dry the rash

Poison Ivy, Oak & Sumac,
Insect Bites, Minor Skin Irritations

Net Wt. 2 oz. (56 g)